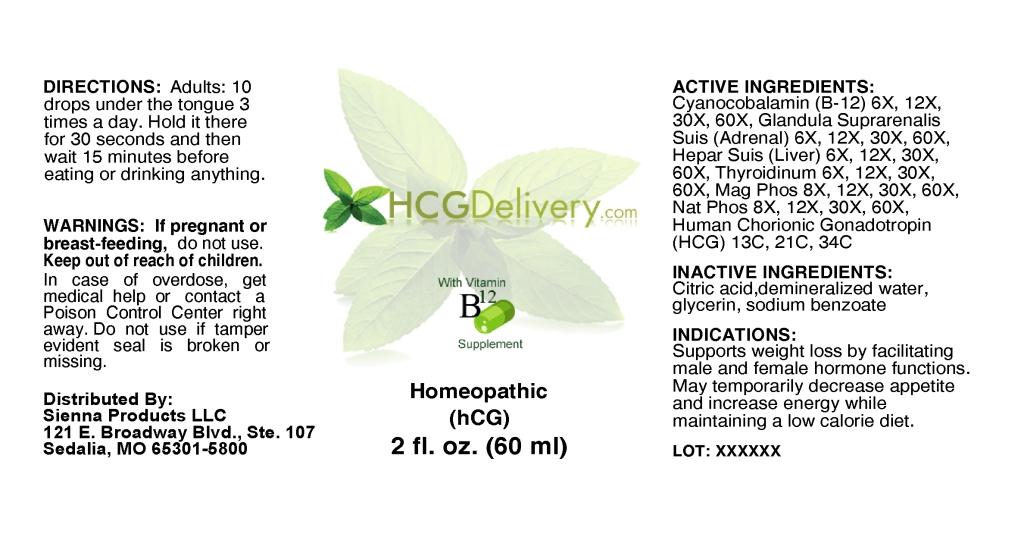 DRUG LABEL: HCGDelivery com
NDC: 57520-0473 | Form: LIQUID
Manufacturer: Apotheca Company
Category: homeopathic | Type: HUMAN OTC DRUG LABEL
Date: 20101210

ACTIVE INGREDIENTS: CYANOCOBALAMIN 60 [hp_X]/1 mL; SUS SCROFA ADRENAL GLAND 60 [hp_X]/1 mL; PORK LIVER 60 [hp_X]/1 mL; SUS SCROFA THYROID 60 [hp_X]/1 mL; MAGNESIUM PHOSPHATE, DIBASIC TRIHYDRATE 60 [hp_X]/1 mL; SODIUM PHOSPHATE, DIBASIC ANHYDROUS 60 [hp_X]/1 mL; HUMAN CHORIONIC GONADOTROPIN 34 [hp_C]/1 mL
INACTIVE INGREDIENTS: CITRIC ACID MONOHYDRATE; GLYCERIN; SODIUM BENZOATE; WATER

HCHDelivery.com

ACTIVE INGREDIENT

ACTIVE INGREDIENTS: Cyanocobalamin (B-12) 6X,12X, 30X, 60X, Glandula suprarenalis suis (adrenal) 6X, 12X, 30X, 60X, Hepar suis (liver) 6X, 12X, 30X, 60X, Thyroidinum 6X, 12X, 30X, 60X, Magnesia phosphorica 8X, 12X, 30X, 60X, Natrum phosphoricum 8X, 12X, 30X, 60X, Human chorionic gonadotropin (HCG) 13C, 21C, 34C.

PURPOSE

INDICATIONS: Supports weight loss by facilitating male and female hormone functions. May temporarily decrease appetite and increase energy while maintaining a low calorie diet.

WARNINGS

WARNINGS: If pregnant or breast-feeding, do not use.

Keep out of reach of children. In case of overdose, get medical help or contact a Poison Control Center right away.

Do not use if tamper evident seal is broken or missing.

DOSAGE AND ADMINISTRATION

DIRECTIONS: Adults: 10 drops under the tongue 3 times a day. Hold it there for 30 seconds and then wait 15 minutes before eating or drinking anything.

INACTIVE INGREDIENT

INACTIVE INGREDIENTS: Citric acid, Demineralized water, Glycerin, Sodium benzoate.

KEEP OUT OF REACH OF CHILDREN. In case of overdose, get medical help or contact a Poison Control Center right away.

INDICATIONS AND USAGE

INDICATIONS: Supports weight loss by facilitating male and female hormone functions. May temporarily decrease appetite and increase energy while maintaining a low calorie diet.

QUESTIONS

Distributed By:

Sienna Products LLC

121 E. Boadway Blvd., Ste. 107

Sedalia, MO 65301-5800

PACKAGE LABEL

HCGDELIVERY com

With Vitamin B12 Supplement

Homeopathic (hCG)

2 f. oz. (60 ml)